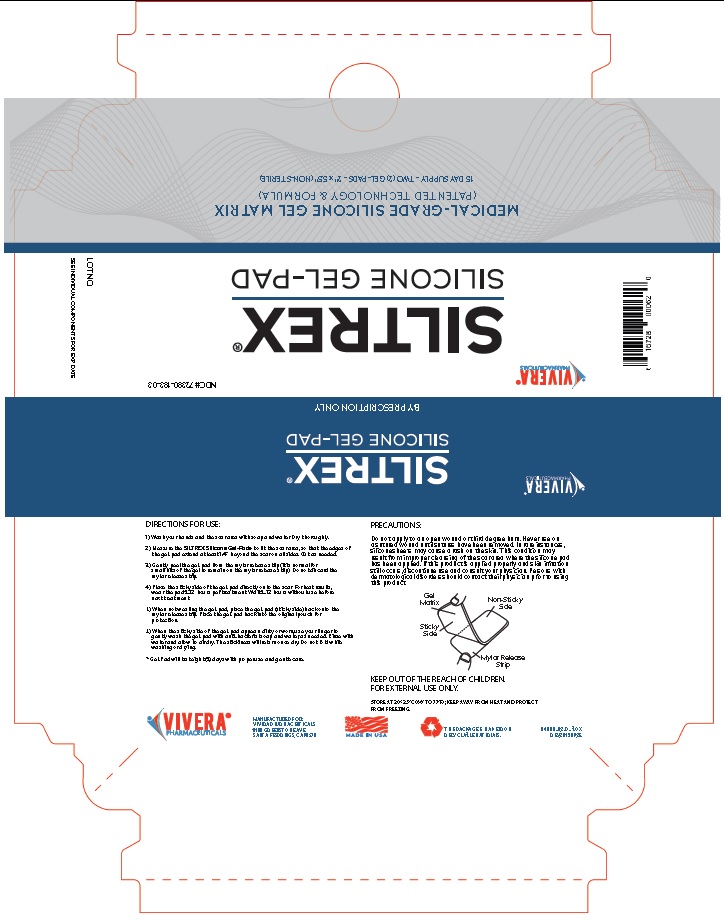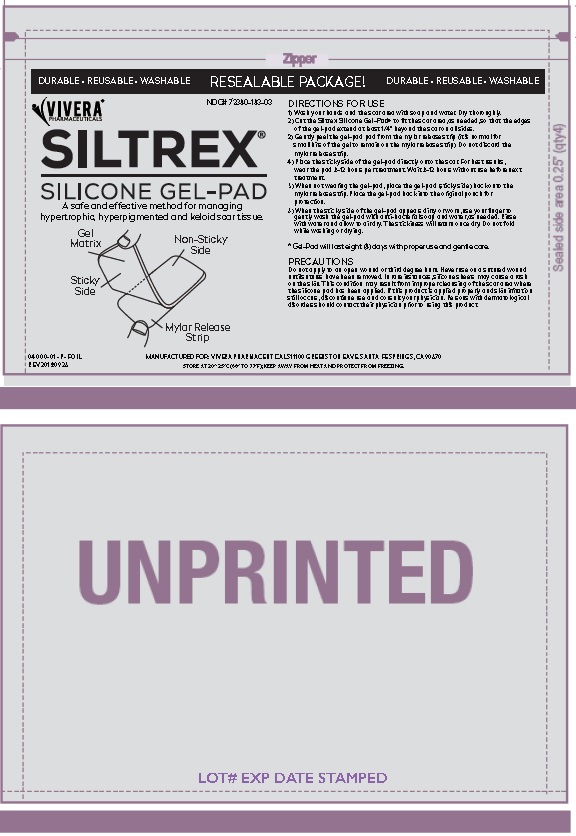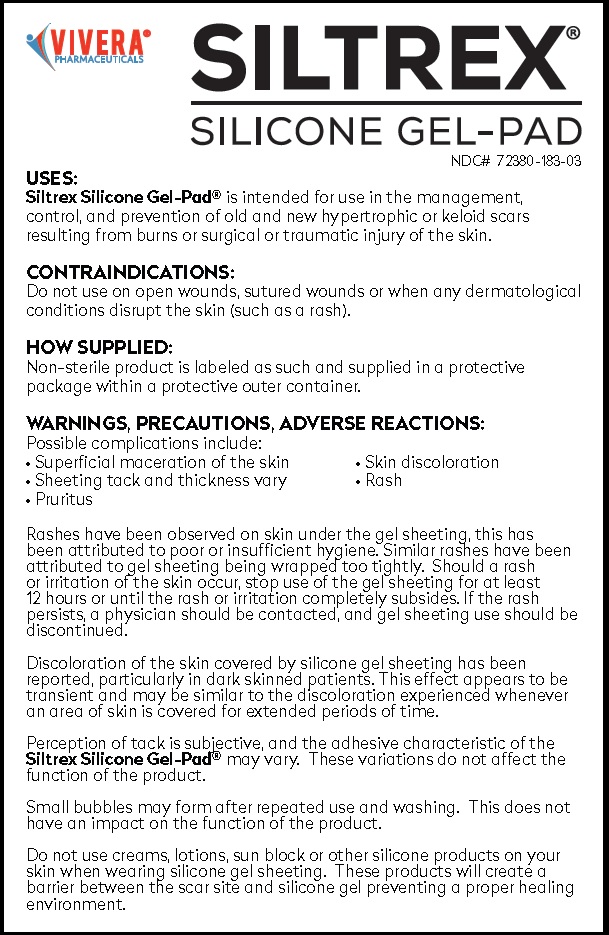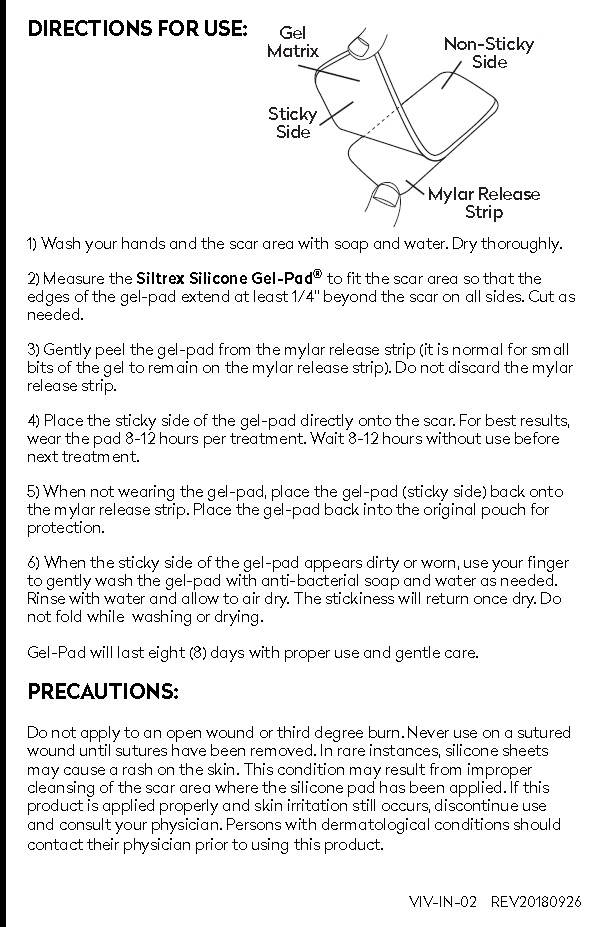 DRUG LABEL: SILTREX SILICONE GEL-PAD
NDC: 72380-183
Manufacturer: Vivera Pharmaceuticals, Inc.
Category: other | Type: MEDICAL DEVICE
Date: 20181015

SILTREX® SILICONE GEL-PAD

SILTREX®
SILICONE GEL-PAD

BY PRESCRIPTION ONLY

USES:
Siltrex Silicone Gel-Pad® is intended for use in the management, control, and prevention of old and new hypertrophic or keloid scars resulting from burns or surgical or traumatic injury of the skin.

HOW SUPPLIED:
Non-sterile product is labeled as such and supplied in a protective package within a protective outer container.

CONTRAINDICATIONS:
Do not use on open wounds, sutured wounds or when any dermatological conditions disrupt the skin (such as a rash).

WARNINGS, PRECAUTIONS, ADVERSE REACTIONS:
Possible complications include:

• Superficial maceration of the skin • Skin discoloration
• Sheeting tack and thickness vary • Rash
• Pruritus

Rashes have been observed on skin under the gel sheeting, this has
been attributed to poor or insufficient hygiene. Similar rashes have been
attributed to gel sheeting being wrapped too tightly. Should a rash
or irritation of the skin occur, stop use of the gel sheeting for at least
12 hours or until the rash or irritation completely subsides. If the rash
persists, a physician should be contacted, and gel sheeting use should be
discontinued.

Discoloration of the skin covered by silicone gel sheeting has been
reported, particularly in dark skinned patients. This effect appears to be
transient and may be similar to the discoloration experienced whenever
an area of skin is covered for extended periods of time.

Perception of tack is subjective, and the adhesive characteristic of the
Siltrex Silicone Gel-Pad® may vary. These variations do not affect the function of
the product.

Small bubbles may form after repeated use and washing. This does not
have an impact on the function of the product.

Do not use creams, lotions, sun block or other silicone products on your
skin when wearing silicone gel sheeting. These products will create a
barrier between the scar site and silicone gel preventing a proper healing
environment.

KEEP OUT OF THE REACH OF CHILDREN.
FOR EXTERNAL USE ONLY.

DOSAGE AND ADMINISTRATION

DIRECTIONS FOR USE:

1) Wash your hands and the scar area with soap and water. Dry thoroughly.

2) Measure the Siltrex Silicone Gel-Pad® to fit the scar area so that the edges of the gel-pad extend at least 1/4” beyond the scar on all sides. Cut as needed.

3) Gently peel the gel-pad from the mylar release strip (it is normal for small bits of the gel to remain on the mylar release strip). Do not discard the mylar release strip.

4) Place the sticky side of the gel-pad directly onto the scar. For best results, wear the pad 8-12 hours per treatment. Wait 8-12 hours without use before next treatment.

5) When not wearing the gel-pad, place the gel-pad (sticky side) back onto the mylar release strip. Place the gel-pad back into the original pouch for protection.

6) When the sticky side of the gel-pad appears dirty or worn, use your finger to gently wash the gel-pad with anti-bacterial soap and water as needed. Rinse with water and allow to air dry. The stickiness will return once dry. Do not fold while washing or drying.
Gel-Pad will last eight (8) days with proper use and gentle care.

PRECAUTIONS:
Do not apply to an open wound or third degree burn. Never use on a sutured
wound until sutures have been removed. In rare instances, silicone sheets
may cause a rash on the skin. This condition may result from improper
cleansing of the scar area where the silicone pad has been applied. If this
product is applied properly and skin irritation still occurs, discontinue use
and consult your physician. Persons with dermatological conditions should
contact their physician prior to using this product.

Principal Display Panel

VIVERA®
PHARMACEUTICALS

SILTREX®
SILICONE GEL-PAD

BY PRESCRIPTION ONLY

VIVERA® NDC# 72380-183-03
PHARMACEUTICALS

SILTREX®
SILICONE GEL-PAD

BY PRESCRIPTION ONLY

LOT NO.

SEE INDIVIDUAL COMPONENTS FOR EXP DATE

MEDICAL-GRADE SILICONE GEL MATRIX
(PATENTED TECHNOLOGY & FORMULA)
15 DAY SUPPLY - TWO (2) GEL-PADS - 2” x 5.5” (NON-STERILE)

DIRECTIONS FOR USE:
1) Wash your hands and the scar area with soap and water. Dry thoroughly.
2) Measure the SILTREX Silicone Gel-Pad® to fit the scar area, so that the edges of
the gel-pad extend at least 1/4” beyond the scar on all sides. Cut as needed.
3) Gently peel the gel-pad from the mylar release strip (it is normal for
small bits of the gel to remain on the mylar release strip). Do not discard the
mylar release strip.
4) Place the sticky side of the gel-pad directly onto the scar. For best results,
wear the pad 8-12 hours per treatment. Wait 8-12 hours without use before
next treatment.
5) When not wearing the gel-pad, place the gel-pad (sticky side) back onto the
mylar release strip. Place the gel-pad back into the original pouch for
protection.
6) When the sticky side of the gel-pad appears dirty or worn, use your finger to
gently wash the gel-pad with anti-bacterial soap and water, as needed. Rinse with
water and allow to air dry. The stickiness will return once dry. Do not fold while
washing or drying.
* Gel-Pad will last eight (8) days with proper use and gentle care.

PRECAUTIONS:
Do not apply to an open wound or third degree burn. Never use on
a sutured wound until sutures have been removed. In rare instances,
silicone sheets may cause a rash on the skin. This condition may
result from improper cleansing of the scar area where the silicone pad
has been applied. If this product is applied properly and skin irritation
still occurs, discontinue use and consult your physician. Persons with
dermatological disorders should contact their physician prior to using
this product.

KEEP OUT OF THE REACH OF CHILDREN.
FOR EXTERNAL USE ONLY.

STORE AT 20°-25°C (68° TO 77°F); KEEP AWAY FROM HEAT AND PROTECT FROM FREEZING.

VIVERA®
PHARMACEUTICALS

MANUFACTURED FOR:
VIVERA PHARMACEUTICALS
11100 GREENSTONE AVE.
SANTA FE SPRINGS, CA 90670

MADE IN USA

THIS PACKAGE IS MADE FROM RECYCLABLE MATERIALS.

04000-02-P-BOX
REV20180925

Product Label - Foil Pack

Zipper

DURABLE • REUSABLE • WASHABLE RESEALABLE PACKAGE! DURABLE • REUSABLE • WASHABLE

VIVERA® NDC# 72380-183-03
PHARMACEUTICALS

SILTREX®
SILICONE GEL-PAD

A safe and effective method for managing
hypertrophic, hyperpigmented and keloid scar tissue.

DIRECTIONS FOR USE:
1) Wash your hands and the scar area with soap and water. Dry thoroughly.
2) Cut the SILTREX Silicone Gel-Pad® to fit the scar area, so that the edges
of the gel-pad extend at least 1/4” beyond the scar on all sides. Cut as needed.
3) Gently peel the gel-pad from the mylar release strip (it is normal for
small bits of the gel to remain on the mylar release strip). Do not discard the
mylar release strip.
4) Place the sticky side of the gel-pad directly onto the scar. For best results,
wear the pad 8-12 hours per treatment. Wait 8-12 hours without use before next
treatment.
5) When not wearing the gel-pad, place the gel-pad (sticky side) back onto the
mylar release strip. Place the gel-pad back into the original pouch for
protection.
6) When the sticky side of the gel-pad appears dirty or worn, use your finger to
gently wash the gel-pad with anti-bacterial soap and water, as needed. Rinse
with water and allow to air dry. The stickiness will return once dry. Do not fold
while washing or drying.

* Gel-Pad will last eight (8) days with proper use and gentle care.

PRECAUTIONS:
Do not apply to an open wound or third degree burn. Never use on
a sutured wound until sutures have been removed. In rare instances,
silicone sheets may cause a rash on the skin. This condition may
result from improper cleansing of the scar area where the silicone pad
has been applied. If this product is applied properly and skin irritation
still occurs, discontinue use and consult your physician. Persons with
dermatological disorders should contact their physician prior to using
this product.

04000-01-P-FOIL
REV20180926

MANUFACTURED FOR: VIVERA PHARMACEUTICALS 11100 GREENSTONE AVE. SANTA FE SPRINGS, CA 90670
STORE AT 20°-25°C (68° TO 77°F); KEEP AWAY FROM HEAT AND PROTECT FROM FREEZING.

UNPRINTED

LOT# EXP DATE STAMPED

Product Label - Patient Insert